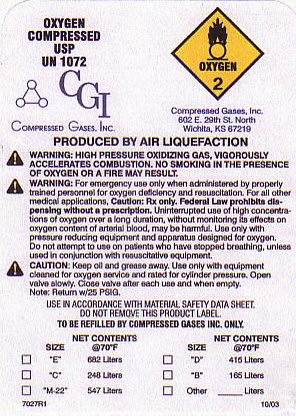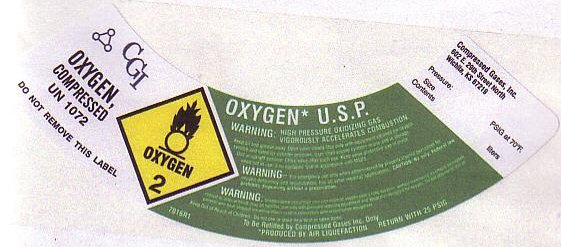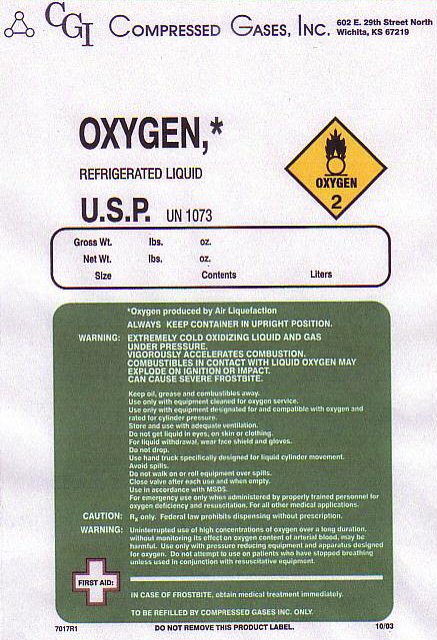 DRUG LABEL: OXYGEN
NDC: 34330-001 | Form: GAS
Manufacturer: Compressed Gases Inc
Category: prescription | Type: HUMAN PRESCRIPTION DRUG LABEL
Date: 20100101

ACTIVE INGREDIENTS: OXYGEN 99 L/100 L

OXYGEN COMPRESSED LABEL

OXYGEN COMPRESSED USP UN 1072 OXYGEN-2 PRODUCED BY AIR LIQUEFACTION.

WARNING: HIGH PRESSURE OXIDIZING GAS, VIGOROUSLY ACCELERATES COMBUSTION. NO SMOKING IN THE PRESENCE OF OXYGEN OR A FIRE MAY RESULT. KEEP OUT OF THE REACH OF CHILDREN.

SIZE________ CONTENTS________________

OXYGEN REFRIGERATED LIQUID LABEL

OXYGEN REFRIGERATED LIQUID U.S.P. UN 1073 OXYGEN-2

GROSS WT________LBS_____OZ

NET WT_____________LBS____OZ

SIZE__________ CONTENTS_____________ LITERS

OXYGEN PRODUCED BY AIR LIQUEFACTION ALWAYS KEEP CONTAINER IN UPRIGHT POSITION.

WARNING: EXTREMELY COLD OXIDIZING LIQUID AND GAS UNDER PRESSURE. VIGOROUSLY ACCELERATES COMBUSTION COMBUSTIBLES IN CONTACT WITH LIQUID OXYGEN MAY EXPLODE ON IGNITION OR IMPACT. CAN CAUSE SEVERE FROSTBITE.

DO NOT DROP. USE HAND TRUCK SPECIFICALLY DESIGNED FOR LIQUID CYLINDER MOVEMENT. AVOID SPILLS. DO NOT WALK ON OR ROLL EQUIPMENT OVER SPILLS

IN CASE OF FROSTBITE OBTAIN MEDICAL TREATMENT IMMEDIATELY.

WARNINGS AND PRECAUTIONS

WARNING: FOR EMERGENCY USE ONLY WHEN ADMINISTERED BY PROPERLY TRAINED PERSONNEL FOR OXYGEN DEFICIENCY AND RESUSCITATION. FOR ALL OTHER MEDICAL APPLICATIONS Rx ONLY.

CAUTION: Rx ONLY. FEDERAL LAW PROHIBITS DISPENSING WITHOUT A PRESCRIPTION. UNINTERRUPTED USE OF HIGH CONCENTRATIONS OF OXYGEN OVER A LONG DURATION WITHOUT MONITORING ITS EFFECT ON OXYGEN CONTENT OF ARTERIAL BLOOD MAY BE HARMFUL. USE ONLY WITH PRESSURE REDUCING EQUIPMENT AND APPARATUS DESIGNED FOR OXYGEN. DO NOT ATTEMPT TO USE ON PATIENTS WHO HAVE STOPPED BREATHING UNLESS USED IN CONJUNCTION WITH RESUSCITATIVE EQUIPMENT.

KEEP OIL AND GREASE AWAY. USE ONLY WITH EQUIPMENT CLEANED FOR OXYGEN SERVICE AND RATED FOR CYLINDER PRESSURE. OPEN VALVE SLOWLY. CLOSE VALVE AFTER EACH USE AND WHEN EMPTY.

NOTE: RETURN WITH 25 PSIG.

USE IN ACCORDANCE WITH MATERIAL SAFETY DATA SHEET. DO NOT REMOVE THIS PRODUCT LABEL.